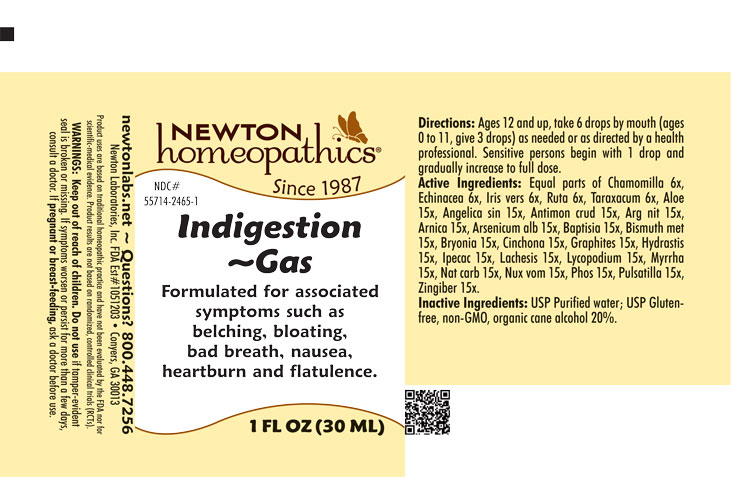 DRUG LABEL: Indigestion-Gas
NDC: 55714-2465 | Form: LIQUID
Manufacturer: Newton Laboratories, Inc.
Category: homeopathic | Type: HUMAN OTC DRUG LABEL
Date: 20250820

ACTIVE INGREDIENTS: MATRICARIA CHAMOMILLA 6 [hp_X]/1 mL; SODIUM CARBONATE 15 [hp_X]/1 mL; IRIS VERSICOLOR ROOT 6 [hp_X]/1 mL; RUTA GRAVEOLENS FLOWERING TOP 6 [hp_X]/1 mL; TARAXACUM OFFICINALE 6 [hp_X]/1 mL; ALOE 15 [hp_X]/1 mL; ANGELICA SINENSIS ROOT 15 [hp_X]/1 mL; ANTIMONY TRISULFIDE 15 [hp_X]/1 mL; SILVER NITRATE 15 [hp_X]/1 mL; ARNICA MONTANA 15 [hp_X]/1 mL; ARSENIC TRIOXIDE 15 [hp_X]/1 mL; CINCHONA OFFICINALIS BARK 15 [hp_X]/1 mL; BAPTISIA TINCTORIA 15 [hp_X]/1 mL; BISMUTH 15 [hp_X]/1 mL; BRYONIA ALBA ROOT 15 [hp_X]/1 mL; GRAPHITE 15 [hp_X]/1 mL; GOLDENSEAL 15 [hp_X]/1 mL; IPECAC 15 [hp_X]/1 mL; LACHESIS MUTA VENOM 15 [hp_X]/1 mL; LYCOPODIUM CLAVATUM SPORE 15 [hp_X]/1 mL; MYRRH 15 [hp_X]/1 mL; PHOSPHORUS 15 [hp_X]/1 mL; ANEMONE PULSATILLA 15 [hp_X]/1 mL; GINGER 15 [hp_X]/1 mL; STRYCHNOS NUX-VOMICA SEED 15 [hp_X]/1 mL; ECHINACEA, UNSPECIFIED 6 [hp_X]/1 mL
INACTIVE INGREDIENTS: WATER; ALCOHOL

Indigestion 2465L

INDICATIONS & USAGE SECTION

Formulated for associated symptoms such as belching, bloating, bad breath, nausea, heartburn and flatulence.

DOSAGE & ADMINISTRATION SECTION

Directions: Ages 12 and up, take 6 drops by mouth (ages 0 to 11, give 3 drops) as needed or as directed by a health professional. Sensitive persons begin with 1 drop and gradually increase to full dose.

OTC - ACTIVE INGREDIENT SECTION

Equal parts of Chamomilla 6x, Echinacea 6x, Iris versicolor 6x, Ruta graveolens 6x, Taraxacum officinale 6x, Aloe 15x, Angelica sinensis radix 15x, Antimonium crudum 15x, Argentum nitricum 15x, Arnica montana 15x, Arsenicum album 15x, Baptisia tinctoria 15x, Bismuthum metallicum 15x, Bryonia 15x, Cinchona officinalis 15x, Graphites 15x, Hydrastis canadensis 15x, Ipecacuanha 15x, Lachesis mutus 15x, Lycopodium clavatum 15x, Myrrha 15x, Natrum carbonicum 15x, Nux vomica 15x, Phosphorus 15x, Pulsatilla 15x, Zingiber officinale 15x.

OTC - PURPOSE SECTION

Formulated for associated symptoms such as belching, bloating, bad breath, nausea, heartburn and flatulence.

INACTIVE INGREDIENT SECTION

Inactive Ingredients: USP Purified Water; USP Gluten-free, non-GMO, organic cane alcohol 20%.

QUESTIONS SECTION

newtonlabs.net - Questions? 800.448.7256

Newton Laboratories, Inc. FDA Est # 1051203 Conyers, GA 30013

WARNINGS SECTION

WARNINGS: Keep out of reach of children. Do not use if tamper-evident seal is broken or missing. If symptoms worsen or persist for more than a few days, consult a doctor. If pregnant or breast-feeding, ask a doctor before use.

OTC - PREGNANCY OR BREAST FEEDING SECTION

If pregnant or breast-feeding, ask a doctor before use.

OTC - KEEP OUT OF REACH OF CHILDREN SECTION

Keep out of reach of children.